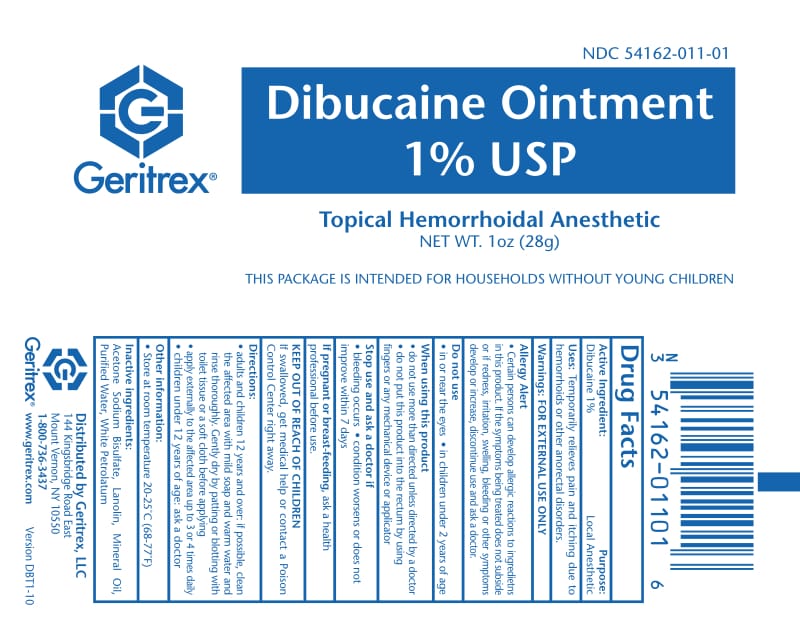 DRUG LABEL: Dibucaine
NDC: 54162-011 | Form: OINTMENT
Manufacturer: GERITREX LLC
Category: otc | Type: HUMAN OTC DRUG LABEL
Date: 20170825

ACTIVE INGREDIENTS: DIBUCAINE 0.28 g/28 g
INACTIVE INGREDIENTS: ACETONE SODIUM BISULFITE; LANOLIN; MINERAL OIL; WATER; PETROLATUM

Dibucaine Ointment

Drug Facts

Active ingredient Purpose

Dibucaine 1% Topical Anesthetic

Uses

For temporary relief of pain and itching associated with sunburn, minor burns, hemorrhoids, cuts, scratches, insect bites, stings

Directions

Not for prolonged use

Adults should not use more than 1oz in 24 hours or 1/4 oz for child

Apply to affected area 3 or 4 times daily

Cover with light dressing, if necessary

Warninigs

For External Use Only

Do not get into the eyes. Stop use and ask a doctor if the condition persists of if rash and irritation develops. you have rectal bleeding

Inactive Ingredients

Aceton Sodium Bisulfate, Lanolin, Mineral Oil, Purified water, White Petrolatum

KEEP OUT OF REACH OF CHILDREN

In the event of accidental ingestion, contact a Poison Control Center right away

STORAGE AND HANDLING

Store at room temperature 15-30'C (59-86'F)

DOSAGE AND ADMINISTRATION

Apply to affected area 3 or 4 times daily